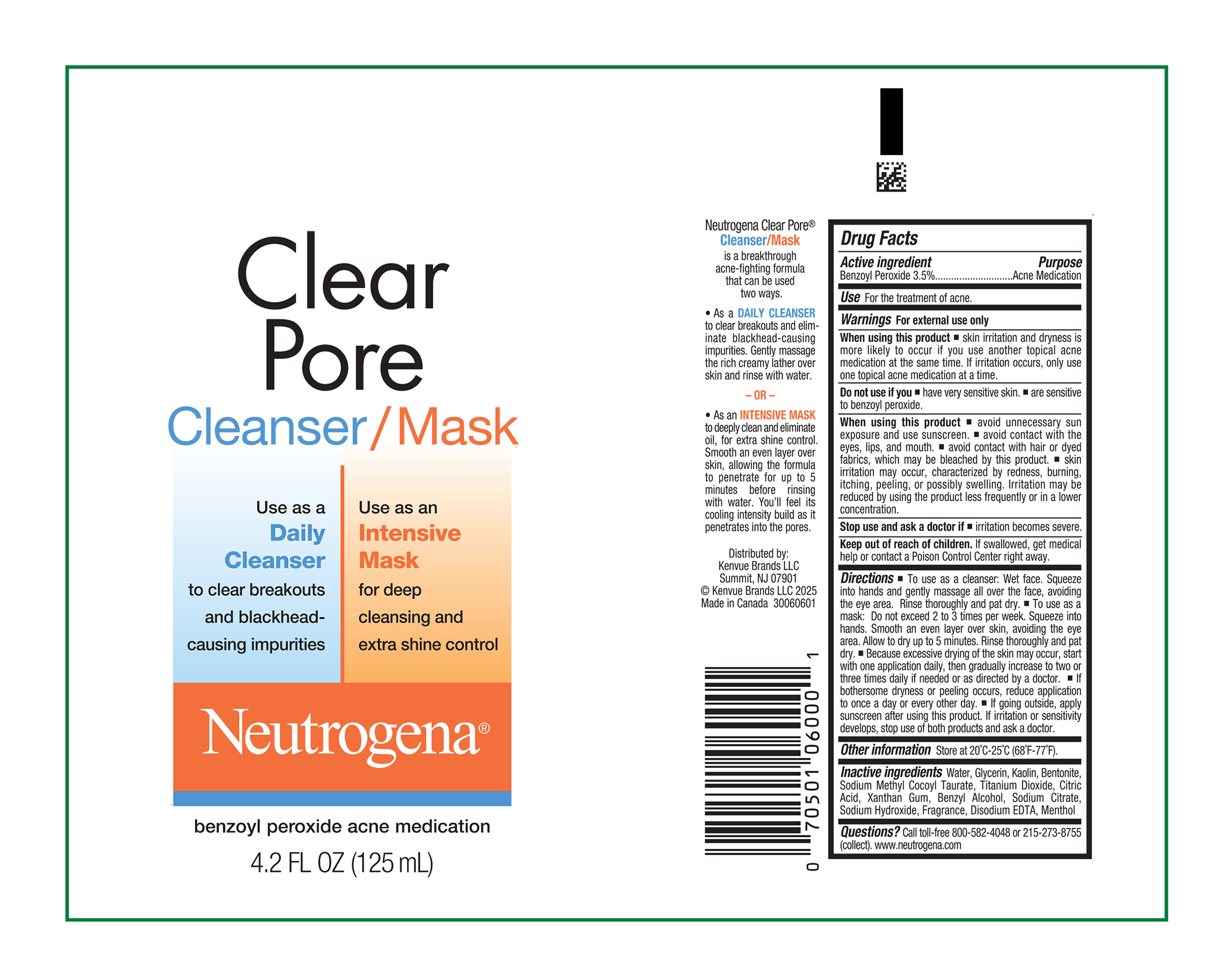 DRUG LABEL: Neutrogena Clear Pore Cleanser Mask
NDC: 69968-0026 | Form: GEL
Manufacturer: Kenvue Brands LLC
Category: otc | Type: HUMAN OTC DRUG LABEL
Date: 20250707

ACTIVE INGREDIENTS: BENZOYL PEROXIDE 35 mg/1 mL
INACTIVE INGREDIENTS: GLYCERIN; KAOLIN; BENTONITE; SODIUM METHYL COCOYL TAURATE; TITANIUM DIOXIDE; CITRIC ACID MONOHYDRATE; XANTHAN GUM; BENZYL ALCOHOL; SODIUM CITRATE, UNSPECIFIED FORM; SODIUM HYDROXIDE; EDETATE DISODIUM; WATER; MENTHOL, UNSPECIFIED FORM

Neutrogena Clear Pore Cleanser Mask

Drug Facts

Active Ingredient

Benzoyl Peroxide (3.5%)

Purpose

.Acne Medication

Use

For the treatment of acne.

Warnings

For external use only.

When using this product

- skin irritation and dryness is more likely to occur if you use another topical acne medication at the same time. If irritation occurs, only use one topical acne medication at a time.

Do not use if you

- have very sensitive skin.
- are sensitive to benzoyl peroxide.

When using this product

- avoid unnecessary sun exposure and use sunscreen.
- avoid contact with the eyes, lips, and mouth.
- avoid contact with hair or dyed fabrics, which may be bleached by this product.
- skin irritation may occur, characterized by redness, burning, itching, peeling, or possibly swelling. Irritation may be reduced by using the product less frequently or in a lower concentration.

Stop use and ask a doctor if

- irritation becomes severe.

Keep out of reach of children. If swallowed, get medical help or contact a Poison Control Center right away.

Directions

- To use as a cleanser: Wet face. Squeeze into hands and gently massage all over the face, avoiding the eye area. Rinse thoroughly and pat dry.
- To use as a mask: Do not exceed 2 to 3 times per week. Squeeze into hands. Smooth an even layer over skin, avoiding the eye area. Allow to dry up to 5 minutes. Rinse thoroughly and pat dry.
- Because excessive drying of the skin may occur, start with one application daily, then gradually increase to two or three times daily if needed or as directed by a doctor.
- If bothersome dryness or peeling occurs, reduce application to once a day or every other day.
- If going outside, apply sunscreen after using this product. If irritation or sensitivity develops, stop use of both products and ask a doctor.

Other Information

Store at 20°C - 25°C (68°F-77°F)

Inactive Ingredients

Water, Glycerin, Kaolin, Bentonite, Sodium Methyl Cocoyl Taurate, Titanium Dioxide, Citric Acid, Xanthan Gum, Benzyl Alcohol, Sodium Citrate, Sodium Hydroxide, Fragrance, Disodium EDTA, Menthol

Questions?

Call toll-free 800-582-4048 or 215-273-8755 (collect). www.neutrogena.com

Distributed by:

Kenvue Brands LLC

Summit, NJ 07901

PRINCIPAL DISPLAY PANEL - 125 mL Tube Label

Clear
Pore
Cleanser/Mask

Use as a
Daily
Cleanser
to clear breakouts
and blackhead-
causing impurities

Use as an
Intensive
Mask
for deep
cleansing and
extra shine control

Neutrogena®
benzoyl peroxide acne medication
4.2 FL OZ (125 mL)